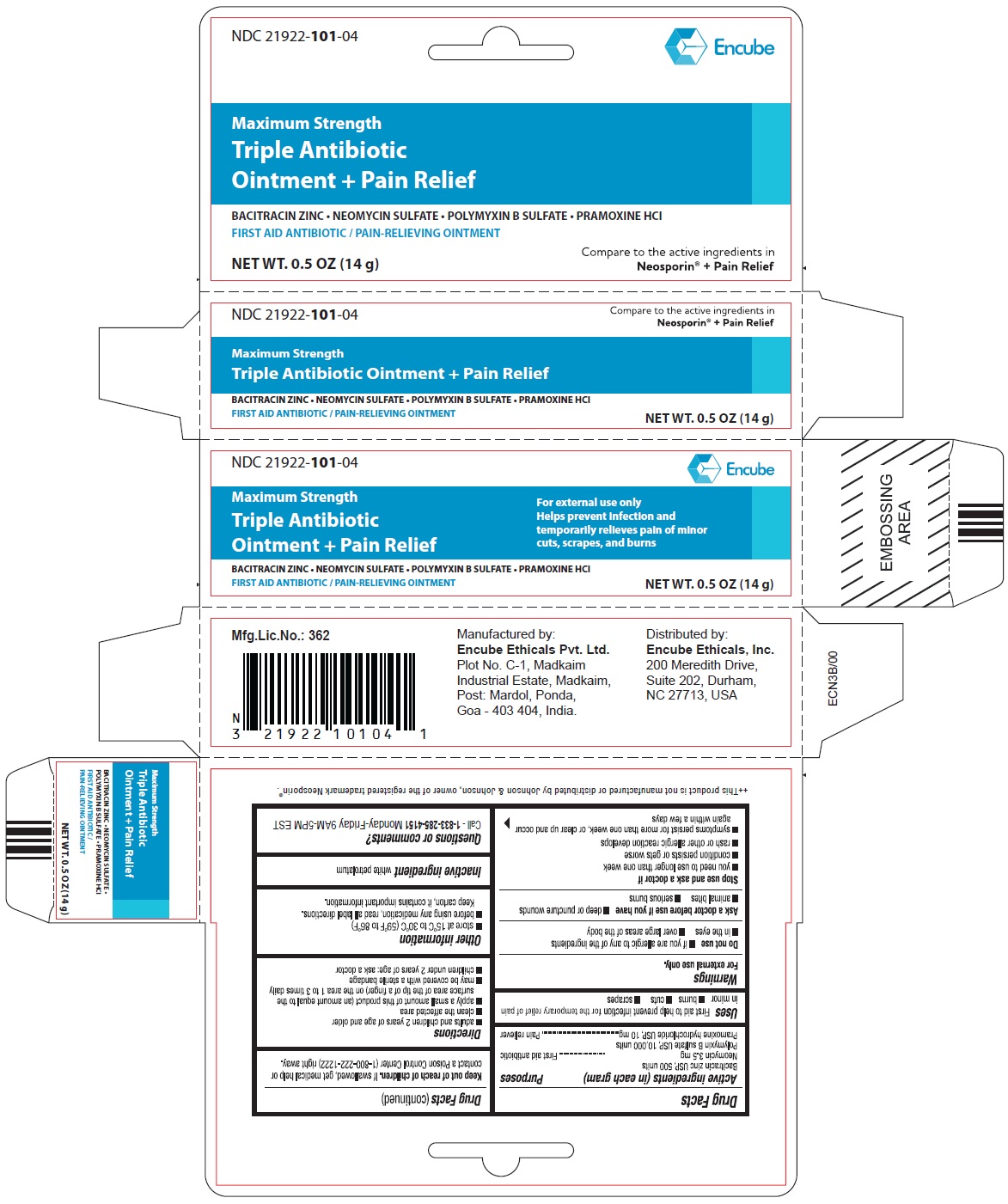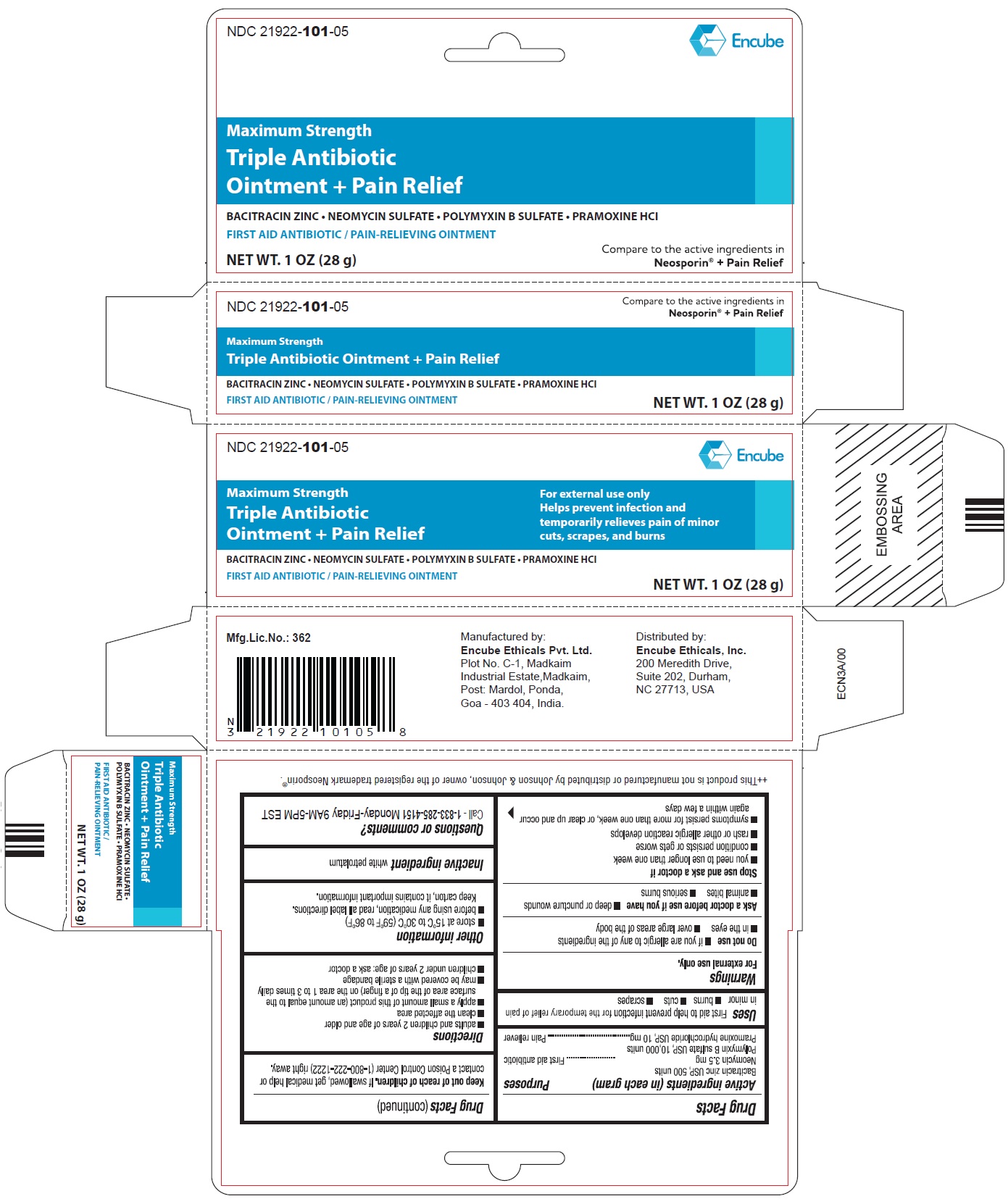 DRUG LABEL: TRIPLE ANTIBIOTIC
NDC: 21922-101 | Form: OINTMENT
Manufacturer: Encube Ethicals, Inc.
Category: otc | Type: HUMAN OTC DRUG LABEL
Date: 20250925

ACTIVE INGREDIENTS: BACITRACIN ZINC 500 [USP'U]/1 g; NEOMYCIN SULFATE 3.5 mg/1 g; POLYMYXIN B SULFATE 10000 [USP'U]/1 g; PRAMOXINE HYDROCHLORIDE 10 mg/1 g
INACTIVE INGREDIENTS: WHITE PETROLATUM

Triple antibiotic ointment + pain relief

Active ingredients (in each gram)

Bacitracin zinc USP, 500 units

Neomycin 3.5 mg

Polymyxin B sulfate USP, 10,000 units

Pramoxine hydrochloride USP, 10 mg

Purposes

First aid antibiotic

Pain reliever

Uses

First aid to help prevent infection for the temporary relief of pain in minor ■ burns ■ cuts ■ scrapes

Warnings

For external use only.

Do not use

■ if you are allergic to any of the ingredients

■ in the eyes

■ over large areas of the body

Ask a doctor before use if you have

■ deeper puncture wounds

■ animal bites

■ serious bums

Stop use and ask doctor if

■ you need to use longer than one week

■ condition persists or gets worse
■ rash or other allergic reaction develops
■ symptoms persist for more than one week, or clear up and occur again within a few days

Keep out of reach of children.

If swallowed, get medical help or contact a Poison Control Center (1-800-222-1222) right away.

Directions

■ adults and children 2 years of age and older
■ clean the affected area
■ apply a small amount of this product (an amount equal to the surface area of the tip of a finger) on the area 1 to 3 times daily
■ may be covered with a sterile bandage
■ children under 2 years of age: ask a doctor

Other information

■ store at 15°G to 30°C (59°F to 86°F)
■ before using any medication, read all label directions. Keep carton, it contains important information.

Inactive ingredient

white petrolatum

Questions or comments?

Call - 1-833-285-4151 Monday-Friday 9AM-5PM EST

PRINCIPAL DISPLAY PANEL

Triple Antibiotic

Ointment + Pain Relief

NET WT. 0.5 OZ (14 g)

Triple Antibiotic

Ointment + Pain Relief

NET WT. 1 OZ (28 g)